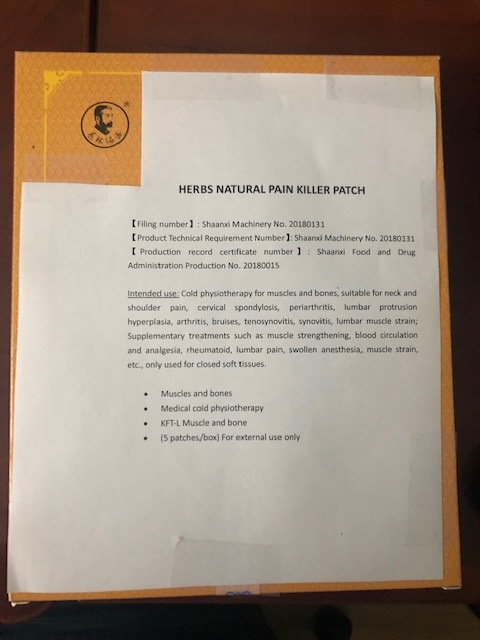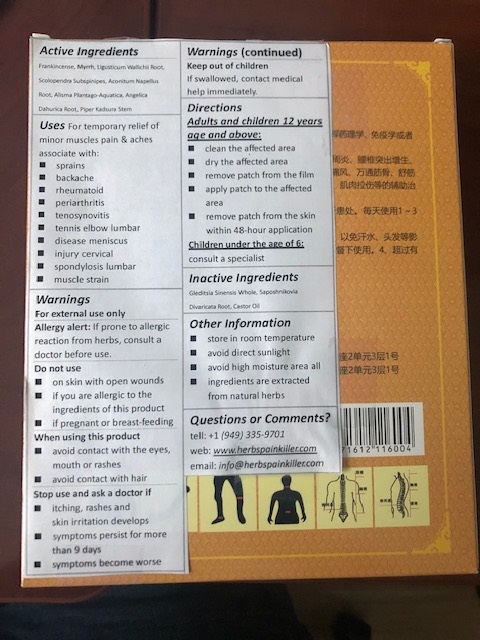 DRUG LABEL: Herbs Natural Pain Killer
NDC: 73585-001 | Form: PATCH
Manufacturer: INNOVATECH CAPITAL CORPORATION
Category: otc | Type: HUMAN OTC DRUG LABEL
Date: 20200408

ACTIVE INGREDIENTS: FRANKINCENSE 3 mg/1 1; MYRRH 3 mg/1 1; LIGUSTICUM WALLICHII ROOT 5 mg/1 1; SCOLOPENDRA SUBSPINIPES 2 mg/1 1; ACONITUM NAPELLUS ROOT 2 mg/1 1; ALISMA PLANTAGO-AQUATICA SUBSP. ORIENTALE ROOT 2 mg/1 1; ANGELICA DAHURICA ROOT 5 mg/1 1; PIPER KADSURA STEM 5 mg/1 1
INACTIVE INGREDIENTS: GLEDITSIA SINENSIS WHOLE; SAPOSHNIKOVIA DIVARICATA ROOT; CASTOR OIL

Active Ingredients

FRANKINCENSE, MYRRH, LIGUSTICUM WALLICHII ROOT, SCOLOPENDRA SUBSPINIPES, ACONITUM NAPELLUS ROOT, ALISMA PLANTAGO-AQUATICA SUBSP. ORIENTALE ROOT, ANGELICA DAHURICA ROOT, PIPER KADSURA STEM

Uses

For temporary relief of minor muscles pain & aches associate with:

- sprains
- backache
- rheumatoid
- periarthritis
- tenosynovitis
- tennis elbow lumbar
- disease meniscus
- injury cervical
- spondylosis lumbar
- muscle strain

Warnings

For external use only

Allergy alert: If prone to allergic reaction from herbs, consult a doctor before use.

Do not use

- on skin with open wounds
- if you are allergic to the ingredients of this product
- if pregnant or breast-feeding

When using this product

- avoid contact with the eyes, mouth or rashes
- avoid contact with hair

Stop use and ask a doctor if

- itching, rashes and excessive skin irritation develops
- symptoms persist for more than 9 days
- symptoms become worse

Directions

Adults and children 12 years age and above:

- clean the affected area
- dry the affected area
- remove patch from the film
- apply patch to the affected area

- remove patch from the skin within 48-hour application

Children under the age of 6: consult a specialist

Other Information

- store in room temperature
- avoid direct sunlight
- avoid high moisture area
- all ingredients are extracted from natural herbs

Inactive Ingredients

GLEDITSIA SINENSIS WHOLE, SAPOSHNIKOVIA DIVARICATA ROOT, CASTOR OIL